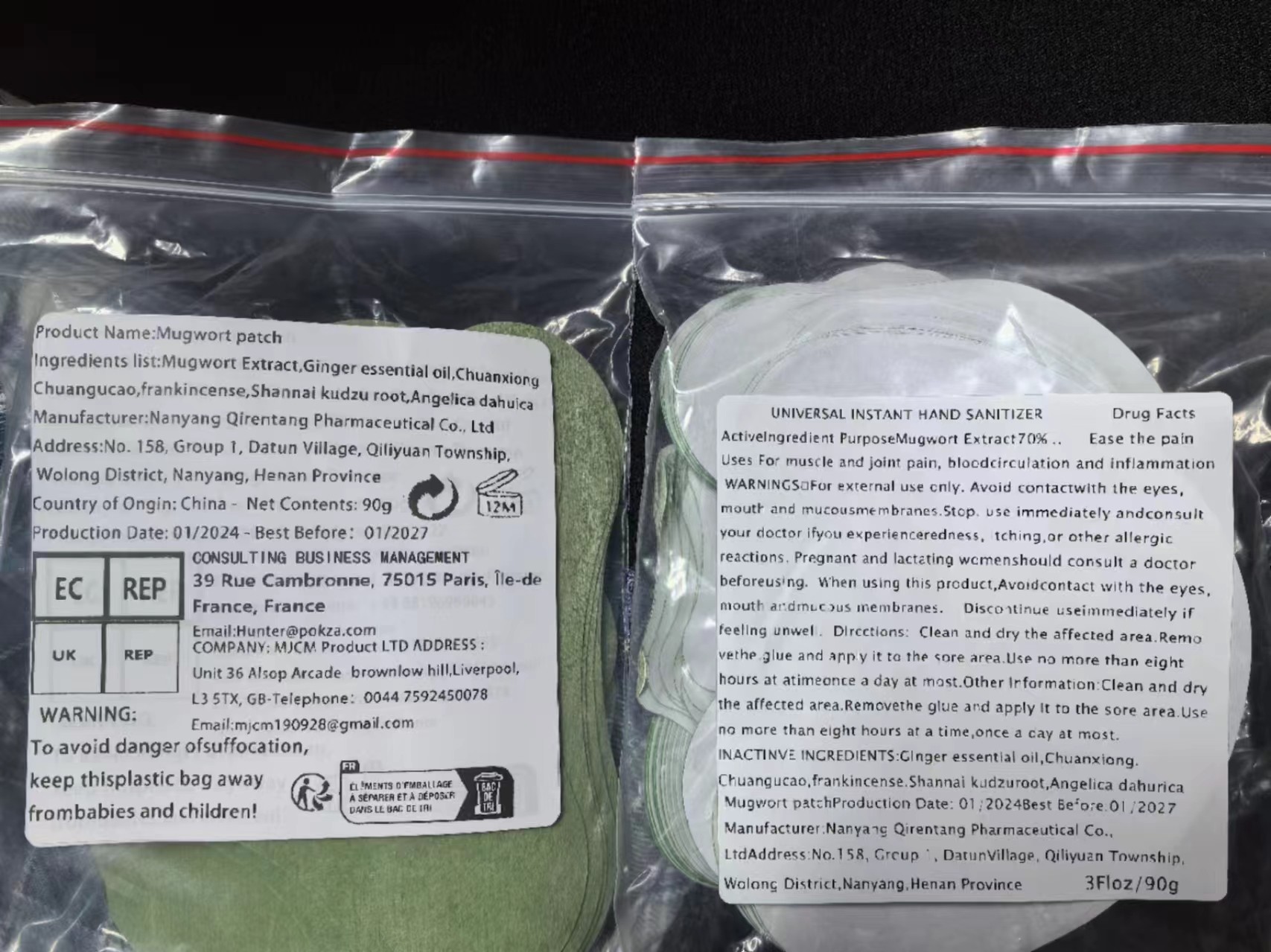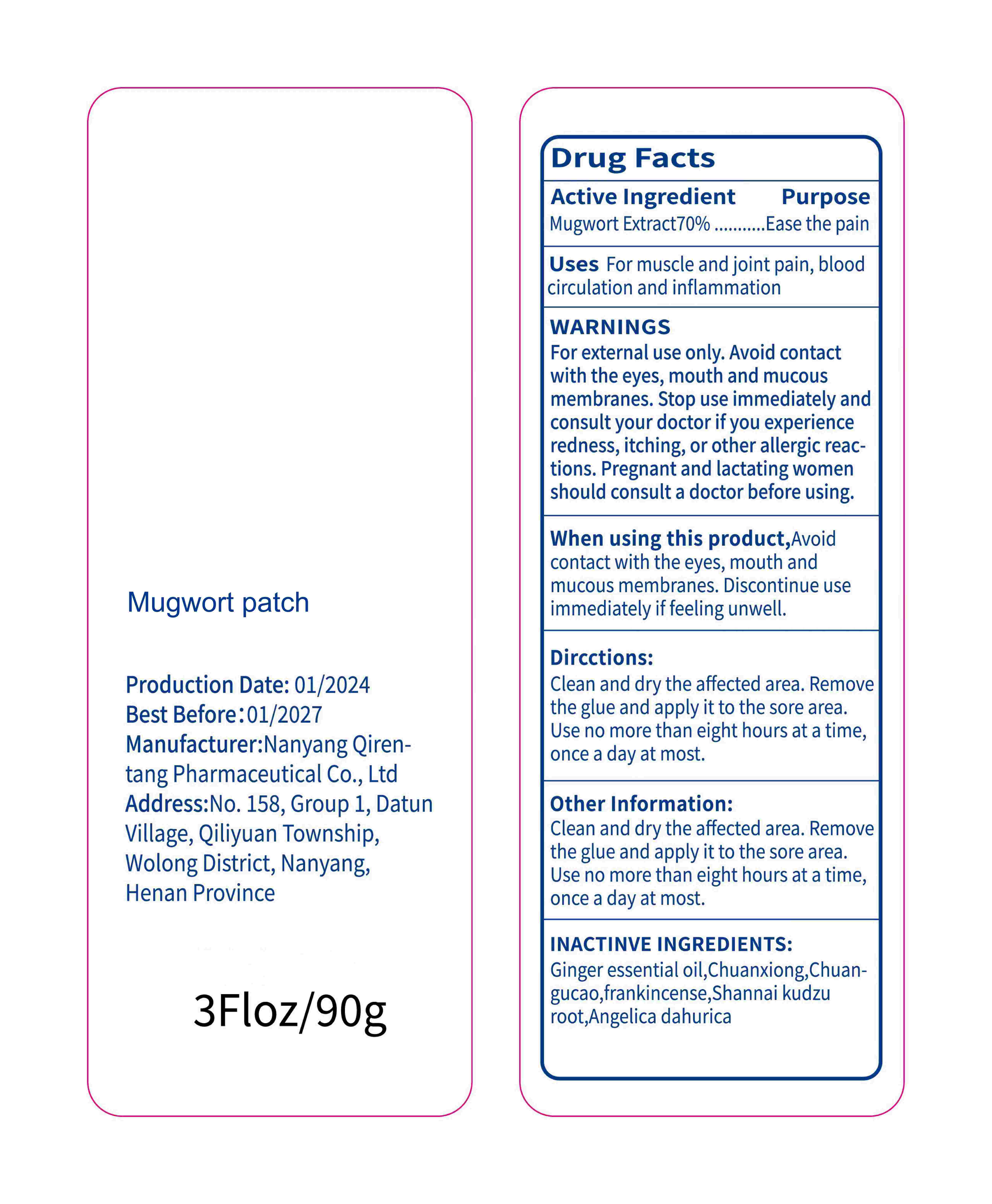 DRUG LABEL: Mugwort patch
NDC: 84640-001 | Form: PATCH
Manufacturer: Yiwu Quyan E-commerce Trading Co., Ltd.
Category: otc | Type: HUMAN OTC DRUG LABEL
Date: 20240813

ACTIVE INGREDIENTS: ARTEMISIA PRINCEPS LEAF 70 g/100 1
INACTIVE INGREDIENTS: ACONITUM CARMICHAELII ROOT; GINGER OIL; LIGUSTICUM SINENSE SUBSP. CHUANXIONG ROOT; FRANKINCENSE; KAEMPFERIA GALANGA ROOT; ANGELICA DAHURICA ROOT

84640-001

Active Ingredient

Mugwort Extract 70%

Purpose

Ease the pain

Use

For muscle and joint pain, blood circulation and inflammation

Warnings

For external use only. Avoid contact with the eyes, mouth and mucous membranes. Stop use immediately and consult your doctor if you experience redness, itching, or other allergic reactions. Pregnant and lactating women should consult a doctor before using.

Do not use

Stop use immediately and consult your doctor if you experience redness, itching, or other allergic reactions.

When Using

Avoid contact with the eyes, mouth and mucous membranes. Discontinue use immediately if feeling unwell.

Stop Use

Stop use immediately and consult your doctor if you experience redness, itching, or other allergic reactions

Ask Doctor

Pregnant and lactating women should consult a doctor before using.

Keep Oot Of Reach Of Children

Please keep this product out of reach of children. If accidentally ingested, please call the emergency center immediately.

Directions

Clean and dry the affected area. Remove the glue and apply it to the sore area. Use no more than eight hours at a time, once a day at most

Other information

Clean and dry the affected area. Remove the glue and apply it to the sore area. Use no more than eight hours at a time, once a day at most

Inactive ingredients

ginger essential oil,Chuanxiong,Chuangucao,frankincense,Shannai kudzu root,Angelica dahurica

Questions

86-15797813020